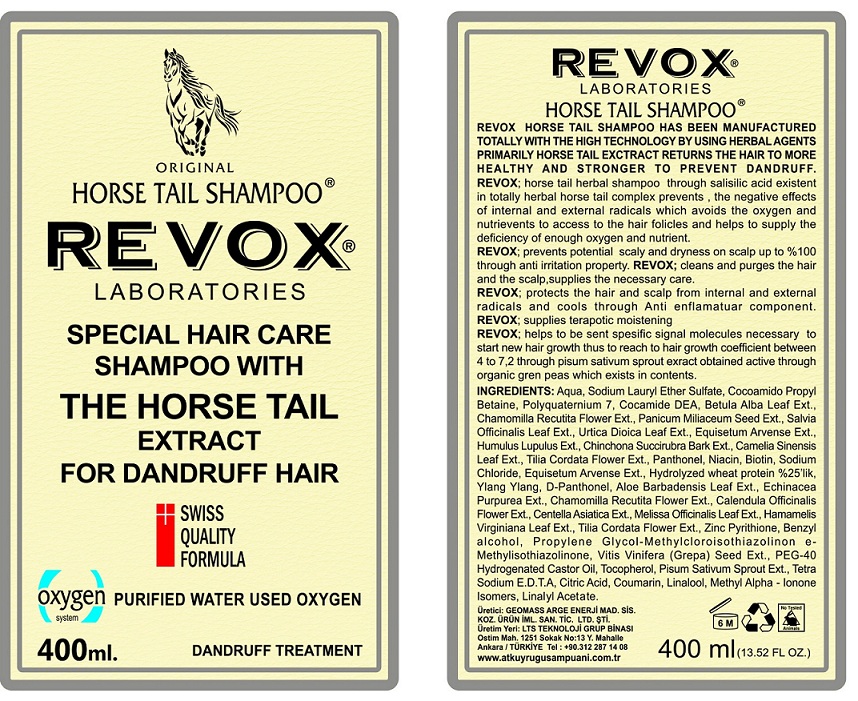 DRUG LABEL: REVOX
NDC: 72029-001 | Form: SHAMPOO
Manufacturer: GEOMASS ARASTIRMA GELISTIRME ENERJI PETROL MADEN SIS ILAC VE KOZ URUN IM SAN TIC LTD STI
Category: otc | Type: HUMAN OTC DRUG LABEL
Date: 20180130

ACTIVE INGREDIENTS: PYRITHIONE ZINC 2 g/100 mL
INACTIVE INGREDIENTS: WATER; SODIUM LAURETH-3 SULFATE; COCAMIDOPROPYL BETAINE; POLYQUATERNIUM-7 (70/30 ACRYLAMIDE/DADMAC; 1600000 MW); COCO DIETHANOLAMIDE; BETULA PUBESCENS LEAF; CHAMOMILE; MILLET; SAGE; URTICA DIOICA LEAF; EQUISETUM ARVENSE BRANCH; HOPS; CINCHONA PUBESCENS BARK; GREEN TEA LEAF; TILIA CORDATA FLOWER; PANTHENOL; NIACIN; BIOTIN; SODIUM CHLORIDE; HYDROLYZED WHEAT PROTEIN (ENZYMATIC, 3000 MW); CANANGA OIL; DEXPANTHENOL; ALOE VERA LEAF; ECHINACEA PURPUREA; CALENDULA OFFICINALIS FLOWER; CENTELLA ASIATICA; MELISSA OFFICINALIS LEAF; HAMAMELIS VIRGINIANA LEAF; BENZYL ALCOHOL; PROPYLENE GLYCOL; METHYLCHLOROISOTHIAZOLINONE; METHYLISOTHIAZOLINONE; VITIS VINIFERA SEED; POLYOXYL 40 HYDROGENATED CASTOR OIL; TOCOPHEROL; PEA; EDETATE SODIUM; ANHYDROUS CITRIC ACID; COUMARIN; LINALOOL, (+/-)-; METHYL-.ALPHA.-IONONE; LINALYL ACETATE

REVOX

Active Ingredient

Zinc Pyrithione

PURPOSE

Anti-dandruff

INDICATIONS AND USAGE

To prevent Dandruff

Prevents potential scaly and dryness on scalp up to 100% through anti-irritation property.

Keep out of reach of children

WARNINGS

For external use only

DOSAGE AND ADMINISTRATION

Massage into scalp and hair. Rinse.

Inactive Ingredients

Aqua, Sodium Lauryl Ether Sulfate, Cocoamido Propyl Betaine, Polyquarternium 7, Cocamide DEA, Betula Alba Leaf Ext., Chamomilla Recutita Flower Ext., Panicum Miliaceum Seed Ext., Salvia Officinalis Leaf Ext., Urtica Dioica Leaf Ext., Equisetum Arvense Ext., Humulus Lupulus Ext., Cinchona Succirubra Bark Ext., Camelia Sinensis Leaf Ext., Tilia Cordata Flower Ext., Panthenol, Niacin, Biotin , Sodium Chloride, Equisetum Arvense Ext., Hydrolyzed Wheat Protein, Ylang Ylang, D-Panthenol, Aloe Barbadensis Leaf Ext., Echinacea Purpurea Ext., Chamomilla Recutita Flower Ext., Calendula Officinalis Flower Ext., Centella Asiatica Ext., Melissa Officinalis Leaf Ext., Hamamelis Virginiana Leaf Ext., Tilia Cordata Flower Ext., Benzyl Alcohol, Propylene Glycol-Methylcloroisothiazolinone- Methylisothiazolinone, Vitis Vinifera (Grape) Seed Ext., PEG- 40 Hydrogenated Castor Oil, Tocopherol, Pisum Sativum Sprout Ext., Tetra Sodium E.D.T.A, Citric Acid, Coumarin, Linalool, Methyl Alpha- Ionone Isomer, Linalyl Acetate.